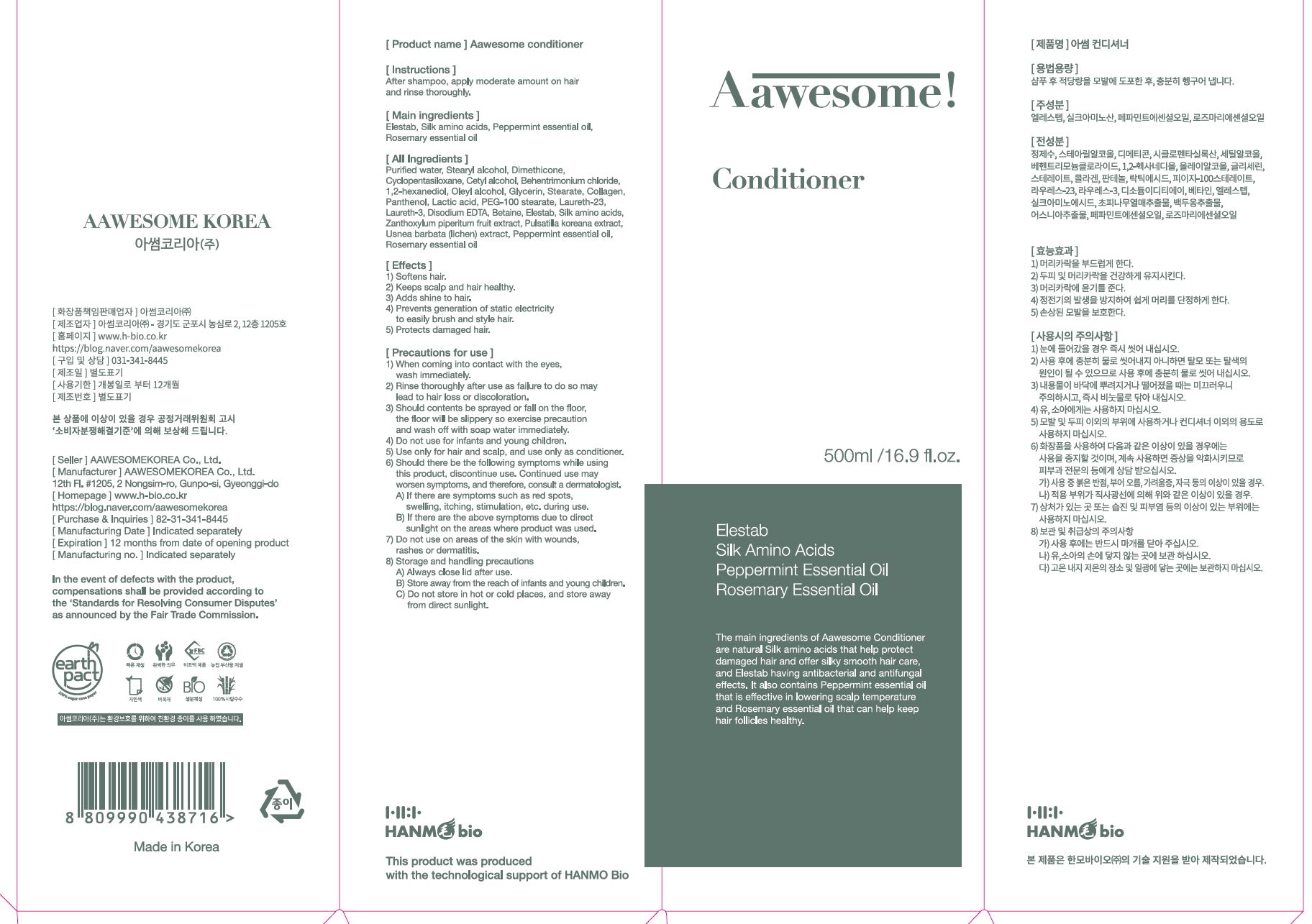 DRUG LABEL: AAWESOME CONDITIONER
NDC: 82483-0002 | Form: LIQUID
Manufacturer: AAWESOMEKOREA Co., Ltd.
Category: otc | Type: HUMAN OTC DRUG LABEL
Date: 20220122

ACTIVE INGREDIENTS: PEPPERMINT OIL 0.1 g/100 mL; AMINO ACIDS, SILK 0.1 g/100 mL; ROSEMARY OIL 0.1 g/100 mL
INACTIVE INGREDIENTS: WATER

ACTIVE INGREDIENT

PEPPERMINT, ROSEMARY, elestab, silk amino acids

PURPOSE

softens hair

keeps scalp and hair healthy

adds shine to hair

prevents generation of static electricity to easily brush and style hair

protects damaged hair

KEEP OUT OF REACH OF THE CHILDREN

WARNINGS

■ For external use only.

■ Do not use in eyes.

■ lf swallowed, get medical help promptly.

■ Stop use, ask doctor lf irritation occurs.

■ Keep out of reach of children.

DOSAGE AND ADMINISTRATION

for external use only

INACTIVE INGREDIENT

water, sodium laureth sulfate, etc

INDICATIONS AND USAGE

after shampoo, apply moderate amount on hair and rinse thoroughly